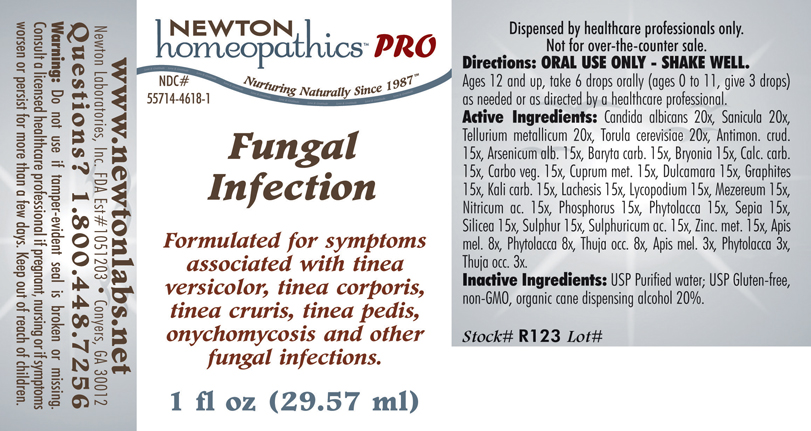 DRUG LABEL: Fungal Infection 
NDC: 55714-4618 | Form: LIQUID
Manufacturer: Newton Laboratories, Inc.
Category: homeopathic | Type: HUMAN PRESCRIPTION DRUG LABEL
Date: 20110601

ACTIVE INGREDIENTS: Candida Albicans 20 [hp_X]/1 mL; Sanicula Europaea Leaf 20 [hp_X]/1 mL; Tellurium 20 [hp_X]/1 mL; Saccharomyces Cerevisiae 20 [hp_X]/1 mL; Antimony Trisulfide 15 [hp_X]/1 mL; Arsenic Trioxide 15 [hp_X]/1 mL; Barium Carbonate 15 [hp_X]/1 mL; Bryonia Alba Root 15 [hp_X]/1 mL; Oyster Shell Calcium Carbonate, Crude 15 [hp_X]/1 mL; Activated Charcoal 15 [hp_X]/1 mL; Copper 15 [hp_X]/1 mL; Solanum Dulcamara Top 15 [hp_X]/1 mL; Graphite 15 [hp_X]/1 mL; Potassium Carbonate 15 [hp_X]/1 mL; Lachesis Muta Venom 15 [hp_X]/1 mL; Lycopodium Clavatum Spore 15 [hp_X]/1 mL; Daphne Mezereum Bark 15 [hp_X]/1 mL; Nitric Acid 15 [hp_X]/1 mL; Phosphorus 15 [hp_X]/1 mL; Phytolacca Americana Root 15 [hp_X]/1 mL; Sepia Officinalis Juice 15 [hp_X]/1 mL; Silicon Dioxide 15 [hp_X]/1 mL; Sulfur 15 [hp_X]/1 mL; Sulfuric Acid 15 [hp_X]/1 mL; Zinc 15 [hp_X]/1 mL; Apis Mellifera 8 [hp_X]/1 mL; Thuja Occidentalis Leafy Twig 8 [hp_X]/1 mL
INACTIVE INGREDIENTS: Alcohol

Fungal Infection

INDICATIONS & USAGE SECTION

FUNGAL INFECTION Formulated for symptoms associated with tinea versicolor, tinea corporis, tinea cruris, tinea pedis, onychomycosis and other fungal infections.

DOSAGE & ADMINISTRATION SECTION

Directions: ORAL USE ONLY - SHAKE WELL. Ages 12 and up, take 6 drops orally (ages 0 to 11, give 3 drops) as needed or as directed by a healthcare professional.

ACTIVE INGREDIENT SECTION

Candida albicans 20x, Sanicula 20x, Tellurium metallicum 20x, Torula cerevisiae 20x, Antimon. crud. 15x, Arsenicum alb. 15x, Baryta carb. 15x, Bryonia 15x, Calc. carb. 15x, Carbo veg. 15x, Cuprum met. 15x, Dulcamara 15x, Graphites 15x, Kali carb. 15x, Lachesis 15x, Lycopodium 15x, Mezereum 15x, Nitricum ac. 15x, Phosphorus 15x, Phytolacca 15x, Sepia 15x, Silicea 15x, Sulphur 15x, Sulphuricum ac. 15x, Zinc. met. 15x, Apis mel. 8x, Phytolacca 8x, Thuja 8x, Apis mel. 3x, Phytolacca 3x, Thuja 3x.

PURPOSE SECTION

Formulated for symptoms associated with tinea versicolor, tinea corporis, tinea cruris, tinea pedis, onychomycosis and other fungal infections.

INACTIVE INGREDIENT SECTION

Inactive Ingredients: USP Purified Water; USP Gluten-free, non-GMO, organic cane dispensing alcohol 20%.

QUESTIONS? SECTION

www.newtonlabs.net Newton Laboratories, Inc. FDA Est # 1051203 -Conyers, GA 30012
Questions? 1.800.448.7256

WARNINGS SECTION

Warning: Do not use if tamper - evident seal is broken or missing. Consult a licensed healthcare professional if pregnant, nursing or if symptoms worsen or persist for more than a few days. Keep out of reach of children.

PREGNANCY OR BREAST FEEDING SECTION

Consult a licensed healthcare professional if pregnant or nursing or if symptoms worsen or persist for more than a few days.

KEEP OUT OF REACH OF CHILDREN SECTION

Keep out of reach of children.